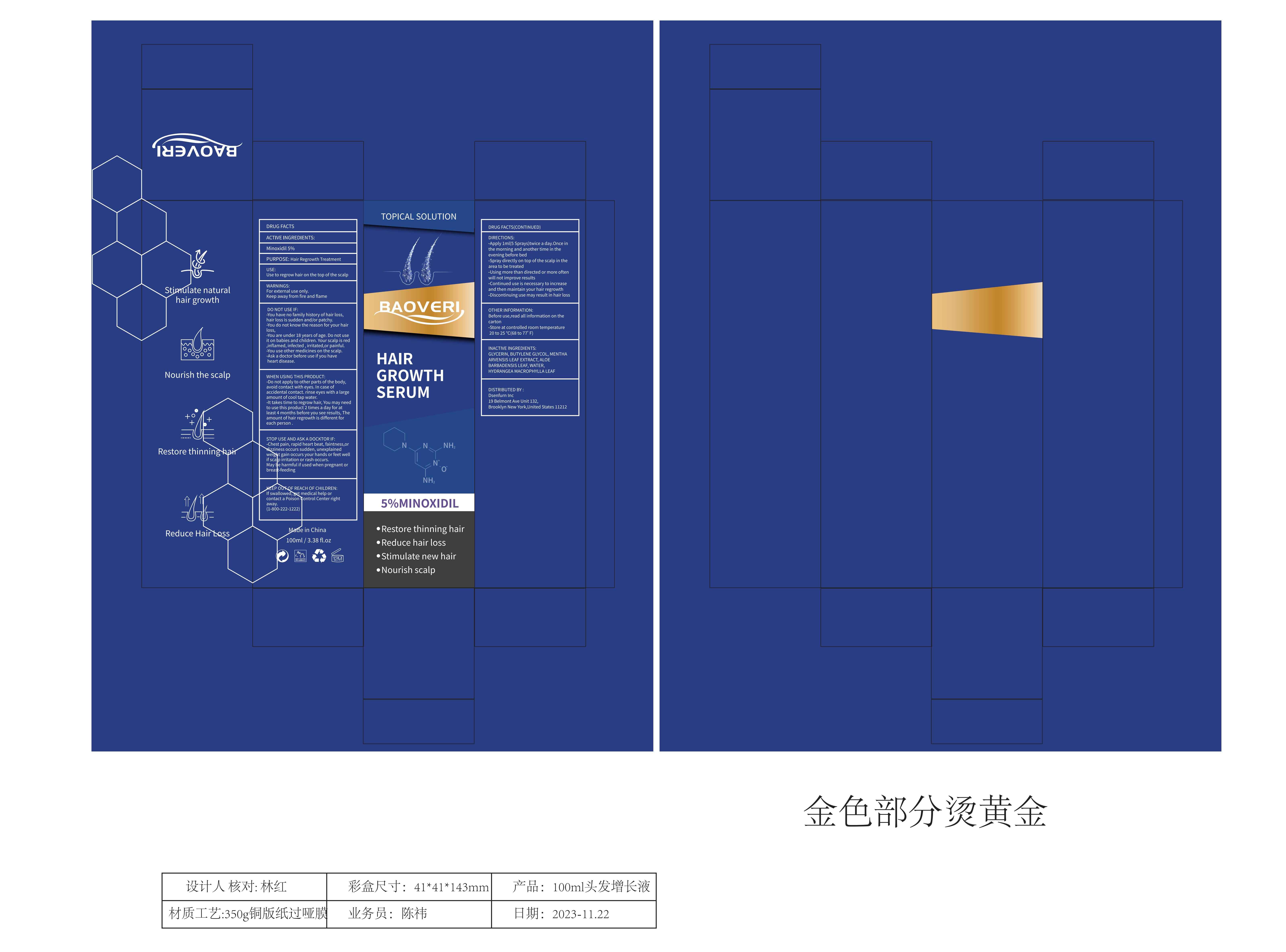 DRUG LABEL: Baoveri Hair growth serum
NDC: 83808-002 | Form: LIQUID
Manufacturer: Shenzhen Pengyun Zhichuang Technology Co., Ltd.
Category: otc | Type: HUMAN OTC DRUG LABEL
Date: 20240425

ACTIVE INGREDIENTS: MINOXIDIL 5 g/100 mL
INACTIVE INGREDIENTS: GLYCERIN; WATER; HYDRANGEA MACROPHYLLA LEAF; ALOE VERA LEAF; BUTYLENE GLYCOL; MENTHA ARVENSIS LEAF

83808-002

Active Ingredient

Minoxidil 5%

Purpose

hair growth

Use

Direct jet the scalp with four sprays from the back to the crown to the frontal region.

When Using

Washing the hair less often will help preserve the oils in the scalp and keep hair well.

If you want to wash your head multiple times per week, don’t use any shampoo, just use water, and massage.

Stop Use

Do not use it if you have the following conditions: Heart sensibility, Super-sensitive skin, an open wound, or after a derma roll since that can cause irritations.

Keep Oot Of Reach Of Children

Please keep this product out of reach of children

Directions

Step 1

For scalp

Direct jet the scalp with four sprays from the back to the crown to the frontal region.

For beard

Direct-jet each cheek with two sprays.

Step 2

Use twice daily on clean hair. Use fingertips to massage the solution into skin/hair for 2-3 minutes. (Apply pressure, so that blood flow can increase for both scalp and beard)

Inactive ingredients

PANTHENOL 1%, TRIPEPTIDE-1 2%, AZELAIC ACID 2%, NIACINAMIDE 2%, MENTHA ARVENSIS LEAF EXTRACT、HYDRANGEA MACROPHYLLA LEAF EXTRACT、ALOEBARBADENSIS LEAF EXTRACT、PORTULACAOLERACEA EXTRACT、 CHRYSANTHELLUMINDICUM EXTRACT、 SOPHORA ANGUSTIFOLIAROOT EXTRACT 5%, CENTELLA ASIATICA ROOT EXTRACT 2%, ALCOHOL 3%, CURCUMIN 0.5%, HYDROLYZED WHEAT PROTEIN 2%, MOROCCAN NUT OIL 2%, ROSA CANINA FRUIT OIL 1%, SODIUM HYALURONATE 1%, BIOTIN 1%, RETINOL 0.025%, HYDROXYACETOPHENONE 0.5%, 1, 2-HEXANEDIOL 0.5%, DISODIUM EDTA 0.05%

Warnings

If you feel uncomfortable, please stop using it immediately